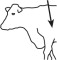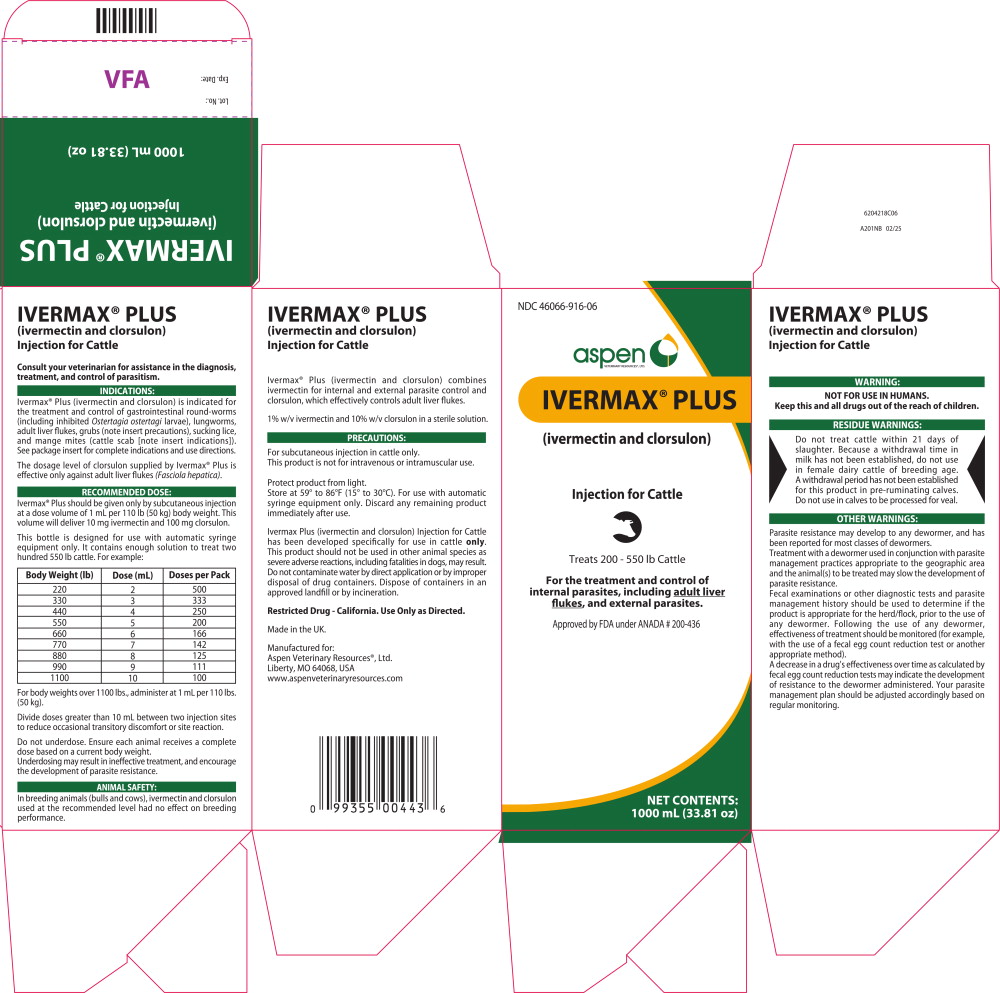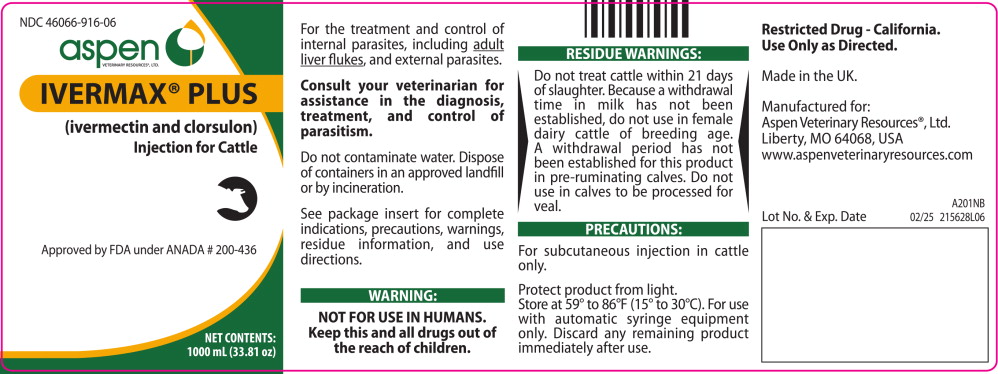 DRUG LABEL: Ivermax Plus for Cattle
NDC: 46066-916 | Form: INJECTION, SOLUTION
Manufacturer: Aspen Veterinary Resources, Ltd.
Category: animal | Type: OTC ANIMAL DRUG LABEL
Date: 20251107

ACTIVE INGREDIENTS: ivermectin 10 mg/1 mL; clorsulon 100 mg/1 mL

IVERMAX® PLUS
(ivermectin and clorsulon)
INJECTION FOR CATTLE

For the effective treatment and control of internal parasites, including adult liver flukes, and external parasites. Consult your veterinarian for assistance in the diagnosis, treatment and control of parasitism.

INTRODUCTION

The ability of ivermectin to deliver internal and external parasite control has been proven in cattle markets around the world. Now, Ivermax® Plus combines ivermectin with clorsulon, an effective adult flukicide.

A single injection of Ivermax® Plus (ivermectin and clorsulon) offers all the benefits of an ivermectin injection plus control of adult Fasciola hepatica.

The dosage level of clorsulon supplied by Ivermax® Plus is effective only against adult liver flukes (Fasciola hepatica).

PRODUCT DESCRIPTION

Ivermax® Plus is a ready-to-use sterile solution containing 1% w/v ivermectin, 10% clorsulon, 40% glycerol formal, and propylene glycol, q.s. ad 100%. It is formulated to deliver the recommended dose level of 200 mcg ivermectin/kg and 2 mg clorsulon/kg given subcutaneously behind the shoulder at the rate of 1 mL per 110 lb (50 kg) body weight.

MODE OF ACTION

Ivermectin is a member of the macrocyclic lactone class of endectocides which have a unique mode of action. Compounds of the class bind selectively and with high affinity to glutamate-gated chloride ion channels which occur in invertebrate nerve and muscle cells. This leads to an increase in the permeability of the cell membrane to chloride ions with hyperpolarization of the nerve or muscle cell, resulting in paralysis and death of the parasite. Compounds of this class may also interact with other ligand-gated chloride channels, such as those gated by the neurotransmitter gamma-aminobutyric acid (GABA).

The margin of safety for compounds of this class is attributable to the fact that mammals do not have glutamate-gated chloride channels, the macrocyclic lactones have a low affinity for other mammalian ligand-gated chloride channels and they do not readily cross the blood-brain barrier.

Clorsulon is rapidly absorbed into the circulating blood.

Erythrocytes with bound drug as well as plasma are ingested by Fasciola hepatica. Adult Fasciola hepatica are killed by clorsulon because of inhibition of enzymes in the glycolytic pathway, which is their primary source of energy.

INDICATIONS

Ivermax® Plus Injection is indicated for the effective treatment and control of the following parasites in cattle:

Gastrointestinal Roundworms (adults and fourth-stage larvae):

Ostertagia ostertagi (including inhibited O. ostertagi)

O. lyrata

Haemonchus placei

Trichostrongylus axei

T. colubriformis

Cooperia oncophora

C. punctata

C. pectinata

Bunostomum phlebotomum

Nematodirus helvetianus (adults only)

N. spathiger (adults only)

Oesophagostomum radiatum

Lungworms (adults and fourth-stage larvae):

Dictyocaulus viviparus

Liver Flukes:

Fasciola hepatica (adults only)

Cattle Grubs (parasitic stages):

Hypoderma bovis

H. lineatum

Sucking Lice:

Linognathus vituli

Haematopinus eurysternus

Solenopotes capillatus

Mange Mites (cattle scab*):

Psoroptes ovis (syn. P. communis var. bovis)

Sarcoptes scabiei var. bovis

Persistent Activity

Ivermectin and clorsulon injection has been proved to effectively control infections and to protect cattle from reinfection with Dictyocaulus viviparus and Oesophagostomum radiatum for 28 days after treatment; Ostertagia ostertagi, Trichostrongylus axei and Cooperia punctata for 21 days after treatment; Haemonchus placei, and Cooperia oncophora for 14 days after treatment.

* Ivermectin has been approved as a scabicide by USDA/APHIS. Federal regulations require that cattle infested with or exposed to scabies (i.e., infestations with Psoroptes ovis) be treated. Ivermectin when used according to label instructions meets this requirement. Treated cattle may be shipped interstate, but they must not be mixed with other cattle for 14 days following treatment. The federal regulations make no restriction on the movement of cattle not affected with or exposed to scabies. However, individual states have additional regulations to govern the interstate shipment of cattle and the regulatory veterinarian in the state of destination should be consulted for applicable regulations on the use of ivermectin in the control of scabies.

DOSAGE

Ivermax® Plus should be given only by subcutaneous injection at a dose volume of 1 mL per 110 lb (50 kg) body weight. This volume will deliver 10 mg ivermectin and 100 mg clorsulon. For example:

Body Weight (lb) | Dose (mL)
220 | 2
330 | 3
440 | 4
550 | 5
660 | 6
770 | 7
880 | 8
990 | 9
1100 | 10

Do not underdose. Ensure each animal receives a complete dose based on a current body weight. Underdosing may result in ineffective treatment, and encourage the development of parasite resistance.

ADMINISTRATION

Ivermax® Plus (ivermectin and clorsulon) Injection is to be given subcutaneously only. Animals should be appropriately restrained to achieve the proper route of administration.

Use of a 16-gauge, 1/2" to 3/4" sterile needle is recommended. Inject the solution subcutaneously (under the skin) behind the shoulder (see illustration)

Any single-dose syringe or standard automatic syringe equipment may be used with the 50 mL or 100 mL pack size. When using the 250 mL, 500 mL or 1000 mL pack size, use only automatic syringe equipment.

Use sterile equipment and sanitize the injection site by applying a suitable disinfectant. Clean, properly disinfected needles should be used to reduce the potential for injection site infections.

No special handling or protective clothing is necessary.

The viscosity of the product increases in cool temperatures. Administering Ivermax® Plus at temperatures of 41 °F (5 °C) or below may be difficult. Users can make dosing easier by warming both the product and injection equipment to about 59 °F (15 °C).

ANIMAL SAFETY

In breeding animals (bulls and cows), ivermectin and clorsulon used at the recommended level had no effect on breeding performance.

WARNING

NOT FOR USE IN HUMANS.

Keep this and all drugs out of the reach of children.

The Safety Data Sheet (SDS) contains more detailed occupational safety information. To report suspected adverse drug events, for technical assistance or to obtain a copy of the SDS, contact 1-866-5777. For additional information about adverse drug experience reporting for animal drugs, contact FDA at 1-888-FDA-VETS or http://www.fda.gov/reportanimalae.

RESIDUE WARNINGS: Do not treat cattle within 21 days of slaughter. Because a withdrawal time in milk has not been established, do not use in female dairy cattle of breeding age. A withdrawal period has not been established for this product in pre-ruminating calves. Do not use in calves to be processed for veal.

PRECAUTIONS

Transitory discomfort has been observed in some cattle following subcutaneous administration. Soft-tissue swelling at the injection site has also been observed. These reactions have disappeared without treatment. Divide doses greater than 10 mL between two injection sites to reduce occasional discomfort or site reaction. Different injection sites should be used for other parenteral products.

Ivermax® Plus Injection has been developed specifically for use in cattle only. This product should not be used in other animal species as severe adverse reactions, including fatalities in dogs, may result.

For subcutaneous injection in cattle only.

This product is not for intravenous or intramuscular use.

When to Treat Cattle with Grubs

Ivermax® Plus effectively controls all stages of cattle grubs. However, proper timing of treatment is important. For most effective results, cattle should be treated as soon as possible after the end of the heel fly (warble fly) season.

Destruction of Hypoderma larvae (cattle grubs) at the period when these grubs are in vital areas may cause undesirable host-parasite reactions including the possibility of fatalities. Killing Hypoderma lineatum when it is in the tissue surrounding the esophagus (gullet) may cause bloat; killing H. bovis when it is in the vertebral canal may cause staggering or paralysis. These reactions are not specific to treatment with Ivermax® Plus, but can occur with any successful treatment of grubs. Cattle should be treated either before or after these stages of grub development. Consult your veterinarian concerning the proper time for treatment.

Cattle treated with Ivermax® Plus after the end of the heel fly season may be retreated with ivermectin during the winter for internal parasites, mange mites, or sucking lice, without danger of grub-related reactions. A planned parasite control program is recommended.

STORAGE

Protect product from light. Store at 59° to 86°F (15° to 30°C). Use within 60 days of first puncture and puncture a maximum of 25 times. If more than 25 punctures are anticipated, the use of multi-dosing equipment is recommended. When using a draw-off spike or needle larger than 16 gauge, discard any remaining product immediately after use. For 500 mL and 1000 mL sizes: For use with automatic syringe equipment only. Discard any remaining product immediately after use.

OTHER WARNINGS

Parasite resistance may develop to any dewormer, and has been reported for most classes of dewormers.

Treatment with a dewormer used in conjunction with parasite management practices appropriate to the geographic area and the animal(s) to be treated may slow the development of parasite resistance.

Fecal examinations or other diagnostic tests and parasite management history should be used to determine if the product is appropriate for the herd/flock, prior to the use of any dewormer. Following the use of any dewormer, effectiveness of treatment should be monitored (for example, with the use of a fecal egg count reduction test or another appropriate method).

A decrease in a drug's effectiveness over time as calculated by fecal egg count reduction tests may indicate the development of resistance to the dewormer administered. Your parasite management plan should be adjusted accordingly based on regular monitoring.

ENVIRONMENTAL SAFETY

Studies indicate that when ivermectin comes in contact with soil it readily and tightly binds to the soil and becomes inactive over time. Free ivermectin may adversely affect fish and certain aquatic organisms. Do not permit water runoff from feedlots to enter lakes, streams, or ponds. Do not contaminate water by direct application or by improper disposal of drug containers. Dispose of containers in an approved landfill or by incineration.

As with other avermectins, ivermectin is excreted in the dung of treated animals and can inhibit the reproduction and growth of pest and beneficial insects that use dung as a source of food and for reproduction. The magnitude and duration of such effects are species and life-cycle specific.

When used according to label directions, the product is not expected to have an adverse impact on populations of dung- dependent insects.

HOW SUPPLIED

Ivermax® Plus Injection is available in five ready-to-use pack sizes:

The 50 mL pack is a multiple-dose, rubber-capped bottle. Each bottle contains sufficient solution to treat 10 head of 550 lb (250 kg) cattle or 100 head of 38 lb (17.3 kg) swine.

The 100 mL pack is a multiple-dose, rubber-capped bottle. Each bottle contains sufficient solution to treat 20 head of 550 lb (250 kg) cattle or 200 head of 38 lb (17.3 kg) swine.

The 250 mL pack is a multiple-dose, rubber-capped bottle. Each bottle contains sufficient solution to treat 50 head of 550 lb (250 kg) cattle or 500 head of 38 lb (17.3 kg) swine.

The 500 mL pack is a multiple-dose, rubber-capped bottle designed for use with automatic syringe equipment. Each bottle contains sufficient solution to treat 100 head of 550 lb (250 kg) cattle or 1000 head of 38 lb (17.3 kg) swine.

The 1000 mL pack is a multiple-dose, rubber-capped bottle designed for use with automatic syringe equipment. Each bottle contains sufficient solution to treat 200 head of 550 lb (250 kg) cattle or 2000 head of 38 lb (17.3 kg) swine.

Restricted Drug - California. Use Only as Directed.

Manufactured for:

Aspen Veterinary Resources®, Ltd.,

Liberty, MO 64068, USA

www.aspenveterinaryresources.com

Made in UK.

Approved by FDA
under ANADA # 200-436

112628I07 A201NB 10/21

aspen
VETERINARY RESOURCES®, LTD

Principal display Panel - 1000 mL Carton Label

NDC 46066-916-06

aspen
VETERINARY RESOURCES®, LTD.

IVERMAX® PLUS

(ivermectin and clorsulon)

Injection for Cattle

Treats 200 - 550 lb Cattle

For the treatment and control of
internal parasites, including adult liver
flukes, and external parasites.

Approved by FDA under ANADA # 200-436

NET CONTENTS:

1000 mL (33.81 fl oz)

Principal display Panel - 1000 mL Bottle Label

NDC 46066-916-06

aspen
VETERINARY RESOURCES®, LTD.

IVERMAX® PLUS

(ivermectin and clorsulon)

Injection for Cattle

Approved by FDA under ANADA # 200-436

NET CONTENTS:

1000 mL (33.81 fl oz)